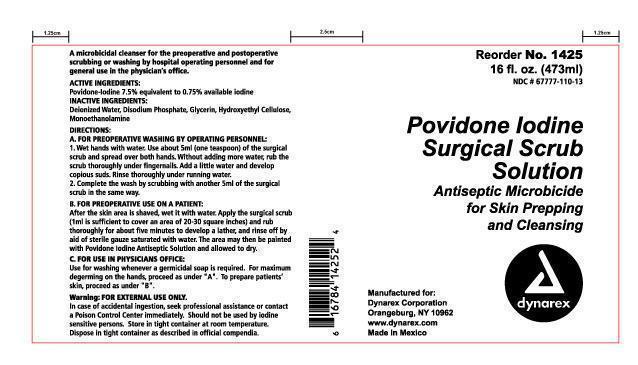 DRUG LABEL: povidine iodine
NDC: 67777-110 | Form: SOLUTION
Manufacturer: Dynarex Corporation
Category: otc | Type: HUMAN OTC DRUG LABEL
Date: 20150106

ACTIVE INGREDIENTS: POVIDONE-IODINE 7.5 mg/1 mL
INACTIVE INGREDIENTS: CITRIC ACID MONOHYDRATE; WATER; GLYCERIN; SODIUM CITRATE; POLYSORBATE 80; SODIUM PHOSPHATE

Povidone Iodine Scrub

Active Ingredient Purpose

Povidone Iodine 7.5% v/v Antiseptic

Inactive Ingredients

Inactive Ingredient: Citric Acid, Glycerin, Sodium Citrate, Tween 80, Disodium Phosphate, Water

Purpose

Purpose of povidone iodine scrub

First aid antiseptic to help prevent skin infection in minor cuts, scrapes and burns.
For preparation of the skin prior to surgery.
Helps reduce bacteria that can potentially cause skin infections.

Warnings:

- FOR EXTERNAL USE ONLY

Do not use:

- As a first aid antiseptic for more than 1 week.
- In the eyes.
- Over large areas of the body.

Ask a doctor before use if you have:

- Deep puncture wounds
- Animal bites
- Serious burns

Stop Use:

- If irritation and redness develop
- If condition persists for more than 72 hours, consult a physician.

Keep out of reach of children.If swallowed, get medical help or contact a Poison Control Center.

Directions:

As a first aid antiseptic

- clean affected area
- apply 1 to 3 times daily
- may be covered with a sterile bandage, if bandaged let dry.

For preoperative patient skin preparation

- clean area
- apply to operative site prior to surgery using the applicator

INDICATIONS AND USAGE

For use as an

- first aid antiseptic
- pre-operative skin preperation

Principal Display Panel

povidone_iodine_scrub